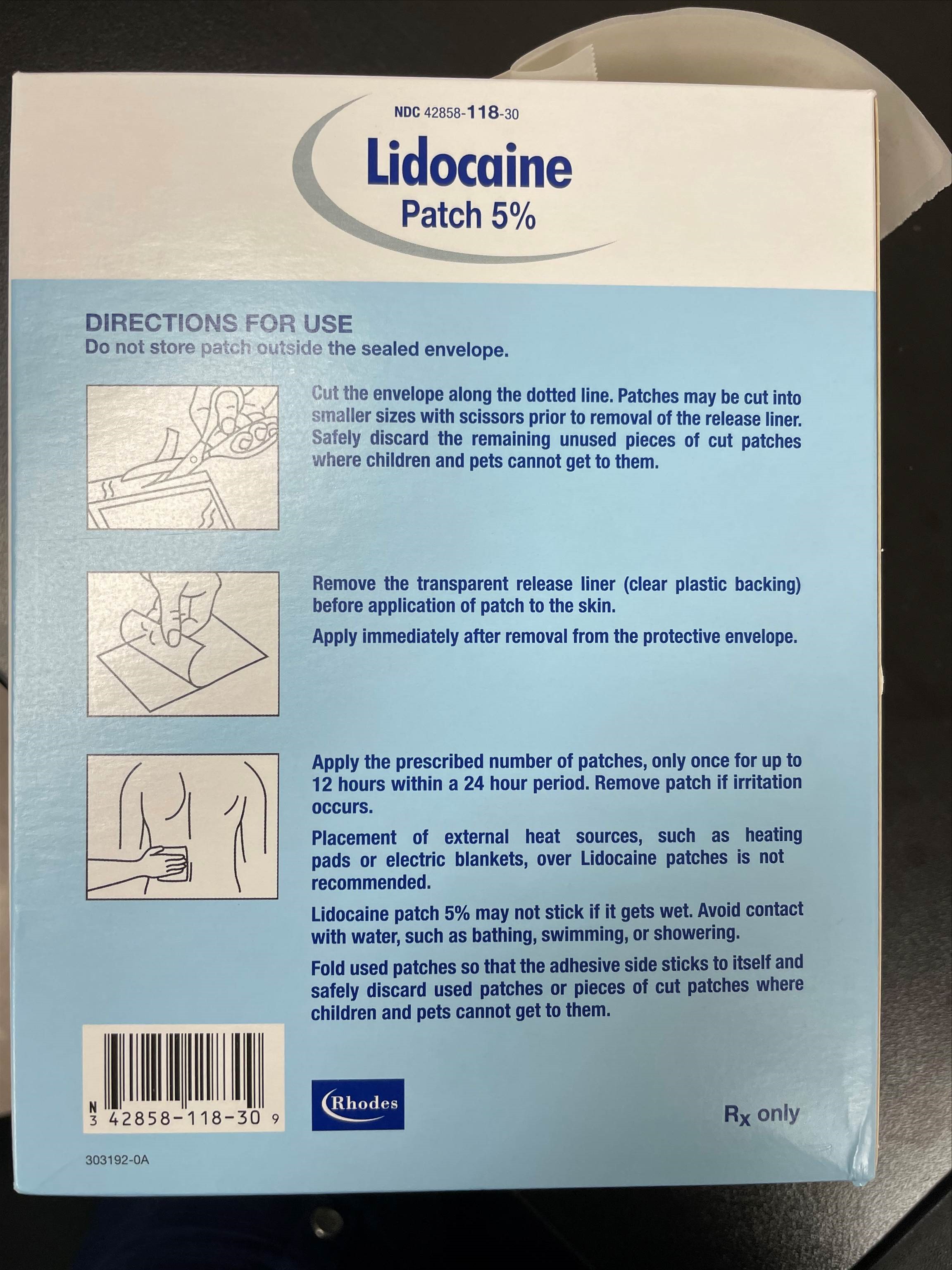 DRUG LABEL: Lidocaine 5%
NDC: 80175-0118 | Form: PATCH
Manufacturer: Central Packaging
Category: prescription | Type: HUMAN PRESCRIPTION DRUG LABEL
Date: 20210211

ACTIVE INGREDIENTS: LIDOCAINE 700 mg/1 1

DOSAGE FORMS AND STRENGTHS

Patch - A drug delivery system that often contains an adhesive backing that is usually applied to an external site on the body. Its ingredients either passively diffuse from, or are actively transported from, some portion of the patch. Depending upon the patch, the ingredients are either delivered to the outer surface of the body or into the body. A patch is sometimes synonymous with the terms ‘extended release film’ and ‘system’.